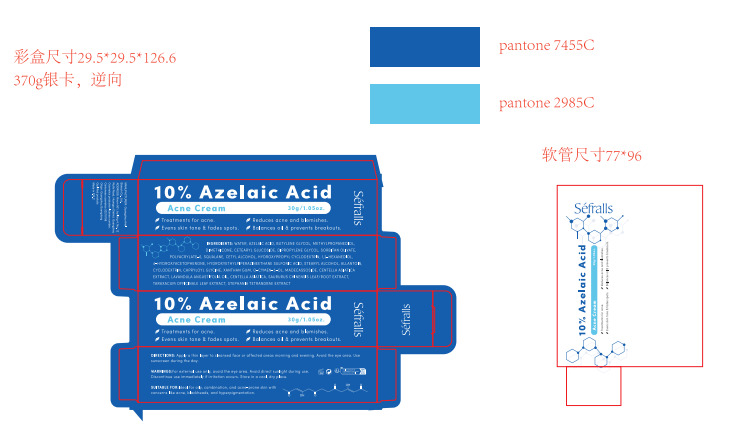 DRUG LABEL: 10% azelaic acid acne cream
NDC: 84148-009 | Form: CREAM
Manufacturer: Guangzhou Ariel Biotech Co., Ltd.
Category: otc | Type: HUMAN OTC DRUG LABEL
Date: 20240929

ACTIVE INGREDIENTS: ASIATICOSIDE 0.015 g/100 g; MADECASSOSIDE 0.055 g/100 g; CENTELLA ASIATICA TRITERPENOIDS 0.03 g/100 g; LAVANDIN OIL 0.03 g/100 g; AZELAIC ACID 10 g/100 g; O-CYMEN-5-OL 0.09 g/100 g; CAPRYLOYL GLYCINE 0.15 g/100 g; HYDROXYETHYLPIPERAZINE ETHANE SULFONIC ACID 0.5 g/100 g; TARAXACUM OFFICINALE LEAF 0.01 g/100 g
INACTIVE INGREDIENTS: BUTYLENE GLYCOL; DIPROPYLENE GLYCOL; METHYLPROPANEDIOL; CETEARYL GLUCOSIDE; CYCLODEXTRINS; ALLANTOIN; HYDROXYACETOPHENONE; WATER; CETYL ALCOHOL; 1,2-HEXANEDIOL; STEARYL ALCOHOL; XANTHAN GUM; SORBITAN OLIVATE; SQUALANE; DIMETHICONE

84148-009

Active Ingredient(s)

AZELAIC ACID 10.00000%

HYDROXYETHYLPIPERAZINE ETHANE SULFONIC ACID 0.50000%

CAPRYLOYL GLYCINE 0.15000%

o-CYMEN-5-OL 0.09000%

MADECASSOSIDE 0.05500%

CENTELLA ASIATICA EXTRACT 0.03000%

LAVANDULA HYBRIDA OIL 0.03000%

ASIATICOSIDE 0.01500%

SAURURUS CHINENSIS LEAF/ROOT EXTRACT 0.01000%

TARAXACUM OFFICINALE (DANDELION) LEAF EXTRACT 0.01000%

STEPHANIA TETRANDRA EXTRACT 0.00160%

Purpose

Acne treatment

①Treatments for acne.
②Reduces acne and blemishes.
③Evens skin tone & fades spots.
④Balances oil & prevents breakouts.

Use

Apply a thin layer to cleansed face or affected areas morning and evening. Avoid the eye area. Use
sunscreen during the day.

Warnings

WARNINGS:For external use only. avoid the eye area. Avoid direct sunlight during use.
Discontinue use immediately if rritation occurs. Store in a cool, dry place.

Do not use

Stop using immediately if there is any stimulation

WHEN USING

Discontinve use if any irritation or adverse reaction occurs.

STOP USE

For external use only, avoid the eye area. Avoid direct sunlight during use. Discontinue use immediately if rritation occurs. Store in a cool, dry place.

Keep out of reach of children.

Directions

Apply a thin layer to cleansed face or affected areas morning and evening. Avoid the eye area. Use sunscreen during the day.

Other information

No Data

Inactive ingredients

WATER, AZEL AIC ACID, BUTYLENE GLYCOL, METHYLPROPANEDIOL, DIMETHICONE, CETEARYL GLUCOSIDE, DIPROPYLENE GLYCOL, SORBITAN OLIVATE, POLYACRYLATE-6, SQUAL ANE, CETYL ALCOHOL, HYDROXYPROPYL CYCLODEXTRIN, 1,2-HEXANEDIOL, 4-HYDROXYACETOPHENONE, HYDROXYETHYLPIPERAZINEETHANE SULFONIC ACID, STEARYL ALCOHOL, ALLANTOIN, CYCLODEXTRIN, CAPRYLOYL GLYCINE, XANTHAN GUM, O-CYMEN-5-OL, MADECASSOSIDE, CENTELLA ASIATICA EXTRACT, LAVANDULA ANGUSTIFOLIA OL, CENTELLA ASIATICA, SAURURUS CHINENSIS LEAF/ROOT EXTRACT, TARAXACUM OFFICINALE LEAF EXTRACT, STEPHANIA TETRANDRAE EXTRACT